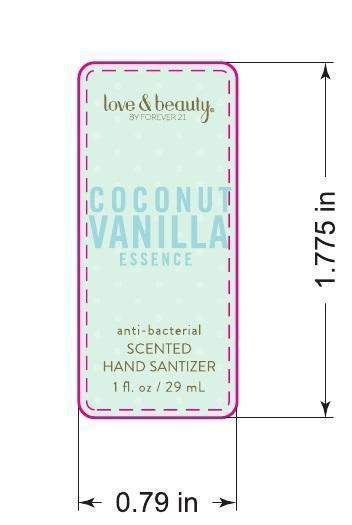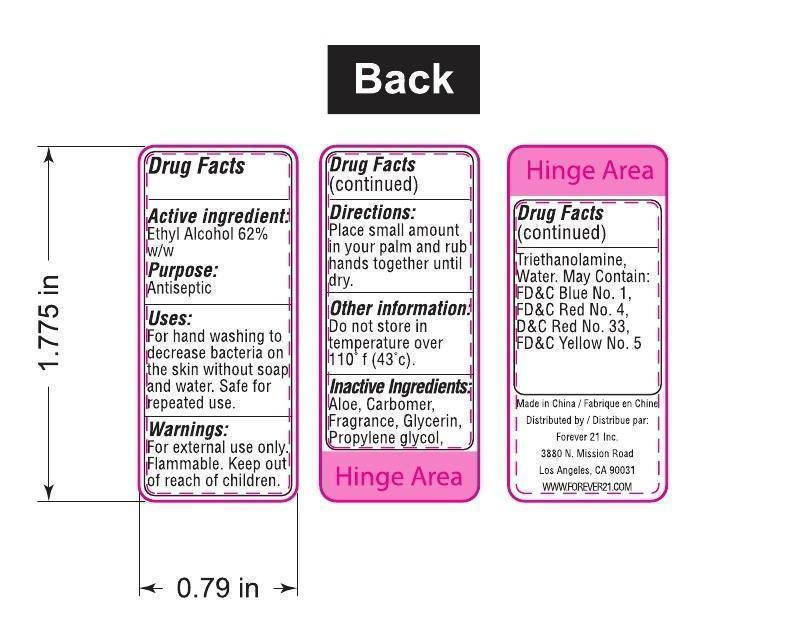 DRUG LABEL: Love and Beauty Coconut Vanilla Essence Antibacterial Scented Hand Sanitizer
NDC: 69290-140 | Form: GEL
Manufacturer: Forever 21
Category: otc | Type: HUMAN OTC DRUG LABEL
Date: 20141017

ACTIVE INGREDIENTS: ALCOHOL 17.98 mL/29 mL
INACTIVE INGREDIENTS: ALOE; CARBOMER INTERPOLYMER TYPE A (ALLYL SUCROSE CROSSLINKED); GLYCERIN; PROPYLENE GLYCOL; TROLAMINE; WATER

Coconut Vanilla Essence Anti-Bacterial Hand Sanitizer by Forever 21

Active Ingredient

Ethyl Alcohol 62% w/w

Purpose

Antiseptic

Uses

For handwashing to decrase bacteria on skin without soap and water. Safe for repeated use.

Warnings

Flammable.

Directions

Place small amount in your palm and rub hands together until dry.

Other Information

Do not store in tempearature over 110 F (43 C).

Inactive Ingredients

Aloe, Carbomer, Fragrance, Glycerin, Propylene Glycol, Triethanolamine, Water. May Contain: FD&C Blue No.1, FD&C Red No 4, D&C Red No.33, FD&C Yellow No.5.

Principal Display Panel

Love & Beauty

By Forever 21

Coconut Vanilla Essence

Anti-Bacterial scented Hand Sanitizer

1 fl. oz / 29 mL

Drug Facts / Information Panel

Made in China / Fabrique en Chine

Distributed by / Distribue par:

Forever 21 Inc

3880 N. Mission Road

Los Angeles, CA 90031

WWW.FOREVER21.COM